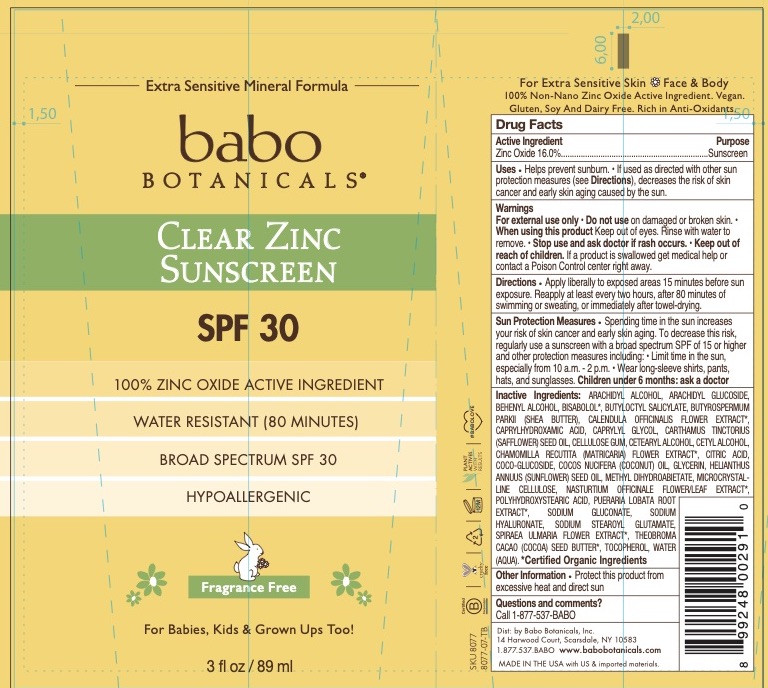 DRUG LABEL: Babo SPF 30 Clear Zinc Fragrance Free
NDC: 79265-8077 | Form: LOTION
Manufacturer: Babo Botanicals, Inc.
Category: otc | Type: HUMAN OTC DRUG LABEL
Date: 20241212

ACTIVE INGREDIENTS: ZINC OXIDE 16 g/100 mL
INACTIVE INGREDIENTS: WATER 50.032 mL/100 mL; COCONUT OIL 5 mL/100 mL; SUNFLOWER OIL 5.1 mL/100 mL; HYALURONATE SODIUM 0.2 mL/100 mL; CETOSTEARYL ALCOHOL 1.3 mL/100 mL; ARACHIDYL GLUCOSIDE 0.306 mL/100 mL; ARACHIDYL ALCOHOL 0.99 mL/100 mL; POLYHYDROXYSTEARIC ACID (2300 MW) 0.25 mL/100 mL; METHYL DIHYDROABIETATE 3 mL/100 mL; NASTURTIUM OFFICINALE FLOWERING TOP 0.002 mL/100 mL; PUERARIA MONTANA VAR. LOBATA ROOT 0.002 mL/100 mL; CALENDULA OFFICINALIS FLOWER 0.002 mL/100 mL; CHAMOMILE 0.002 mL/100 mL; CITRIC ACID MONOHYDRATE 0.2 mL/100 mL; SODIUM STEAROYL GLUTAMATE 1.3 mL/100 mL; CARBOXYMETHYLCELLULOSE SODIUM, UNSPECIFIED FORM 0.14 mL/100 mL; COCOA BUTTER 0.8 mL/100 mL; DOCOSANOL 0.504 mL/100 mL; LEVOMENOL 0.3 mL/100 mL; FILIPENDULA ULMARIA FLOWER 0.002 mL/100 mL; TOCOPHEROL 0.75 mL/100 mL; CELLULOSE, MICROCRYSTALLINE 1.06 mL/100 mL; SODIUM GLUCONATE 0.2 mL/100 mL; SHEA BUTTER 2.1 mL/100 mL; CAPRYLHYDROXAMIC ACID 0.15 mL/100 mL; CAPRYLYL GLYCOL 0.7 mL/100 mL; SAFFLOWER OIL 3 mL/100 mL; BUTYLOCTYL SALICYLATE 5 mL/100 mL; CETYL ALCOHOL 0.75 mL/100 mL; COCO GLUCOSIDE 0.7 mL/100 mL; GLYCERIN 0.158 mL/100 mL

79265-8077 Babo SPF 30 Clear Zinc, Fragrance Free Sunscreen Lotion

79265-8077 SPF 30 Clear Zinc, Fragrance Free Sunscreen Lotion

79265-8077-3 3 fl. oz.

This is an OTC Sunscreen product manufactured pursuant to the sunscreen final monograph, Part352.

Active Ingredients

Zinc Oxide 16.0%

Purpose

Purpose: Sunscreen

Stop use and ask doctor if rash occurs.

Warnings

For external use only • Do not use on damaged or broken skin. • When using this product Keep out of eyes. Rinse with water to remove. • Stop use and ask doctor if rash occurs. • Keep out of reach of children. If a product is swallowed get medical help or contact a Poison Control center right away.

Keep out of reach of children. If a product is swallowed get medical help or contact a Poison Control center right away.

Directions

Apply liberally to exposed areas 15 minutes before sun exposure. Reapply at least every two hours, after 80 minutes of swimming or sweating, or immediately after towel-drying.

Sun Protection Measures• Spending time in the sun increases your risk of skin cancer and early skin aging. To decrease this risk, regularly use a sunscreen with a broad spectrum SPF of 15 or higher and other protection measures including: • Limit time in the sun, especially from 10 a.m. - 2 p.m. • Wear long-sleeve shirts, pants, hats, and sunglasses. Children under 6 months: ask a doctor

Inactive Ingredients

ARACHIDYL ALCOHOL, ARACHIDYL GLUCOSIDE, BEHENYL ALCOHOL, BISABOLOL*, BUTYLOCTYL SALICYLATE, BUTYROSPERMUM PARKII (SHEA BUTTER), CALENDULA OFFICINALIS FLOWER EXTRACT*, CAPRYLHYDROXAMIC ACID, CAPRYLYL GLYCOL, CARTHAMUS TINCTORIUS (SAFFLOWER) SEED OIL, CELLULOSE GUM, CETEARYL ALCOHOL, CETYL ALCOHOL, CHAMOMILLA RECUTITA (MATRICARIA) FLOWER EXTRACT*, CITRIC ACID, COCO-GLUCOSIDE, COCOS NUCIFERA (COCONUT) OIL, GLYCERIN, HELIANTHUS ANNUUS (SUNFLOWER) SEED OIL, METHYL DIHYDROABIETATE, MICROCRYSTAL-LINE CELLULOSE, NASTURTIUM OFFICINALE FLOWER/LEAF EXTRACT*, POLYHYDROXYSTEARIC ACID, PUERARIA LOBATA ROOT EXTRACT*, SODIUM GLUCONATE, SODIUM HYALURONATE, SODIUM STEAROYL GLUTAMATE, SPIRAEA ULMARIA FLOWER EXTRACT*, THEOBROMA CACAO (COCOA) SEED BUTTER*, TOCOPHEROL, WATER (AQUA). *Certified Organic Ingredients

Other Information

Protect this product from excessive heat and direct sun

Questions and comments?Call 1-877-537-BABO

Information Panel

Dist: by Babo Botanicals, Inc.

14 Harwood Court, Scarsdale, NY 10583

1.877.537.BABO www.babobotanicals.com

MADE IN THE USA with US & imported materials.

Uses

Helps prevent sunburn. • If used as directed with other sun protection measures (see Directions), decreases the risk of skin cancer and early skin aging caused by the sun.

Principal Display Panel

Babo Botanicals

Clear Zinc Sunscreen

Broad Spectrum SPF 30

Hypoallergenic

Fragrance Free

For Babies, Kids & Grown Ups Too!

3 fl oz / 89 ml